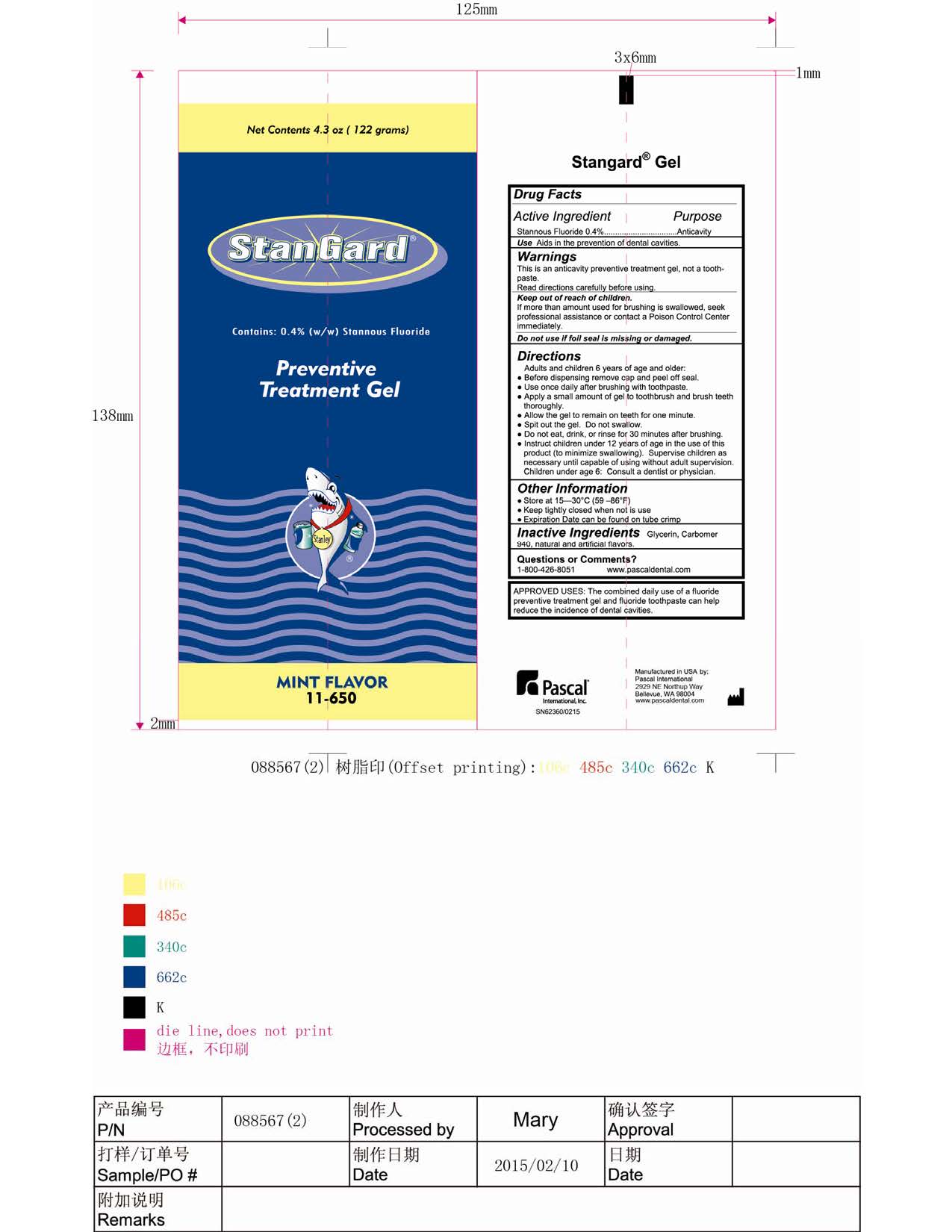 DRUG LABEL: Stangard
NDC: 10866-0271 | Form: GEL
Manufacturer: Pascal Company, Inc.
Category: prescription | Type: HUMAN PRESCRIPTION DRUG LABEL
Date: 20221219

ACTIVE INGREDIENTS: STANNOUS FLUORIDE 3.8 mg/1 g
INACTIVE INGREDIENTS: CARBOMER HOMOPOLYMER TYPE C 12.56 mg/1 g

Stangard Preventive Treatment Gel

Active Ingredient:

Active Ingredient: Stannous Fluoride 0.4%

Purpose: Anticavity

Warnings:

This is an anticavity preventive treatmeng gel, not a toothpaste.

Read directions carefully before using

Keep out of reach of children

If more than amount used for brushing is swallowed, seek professional assistance or contact a Poison Control Center immediately.

Do not use if foil seal is missing or damaged.

Directions

Adults and children 6 years of age and older:

Before dispensing, remove cap and peel off seal

Use once daily after brushing with toothpaste

Apply a small amount of gel totoothbrush and brush teeth thoroughly

Allow the gel to remain on teeth for one minute

Spit out the gel. Do not swallow.

Do not eat, drink or rinse for 30 minutes after brushing

Instruct children under 12 years of age in the use of this product (to minimize swallowing). Supervise children as necessary until capable of using without adult supervision.

Children under age 6: Consult a dentist or physician.

Inactive Ingredients

Glycerin, carbomer 940, natural and artificial flavors

Other Information:

Store at 15-30°C (59-86ºF)

Keep tightly closed when not in use

Expiration Date can be found on tube crimp

StanGard

StanGard Preventive Treatment Gel Mint Flavor 11-650